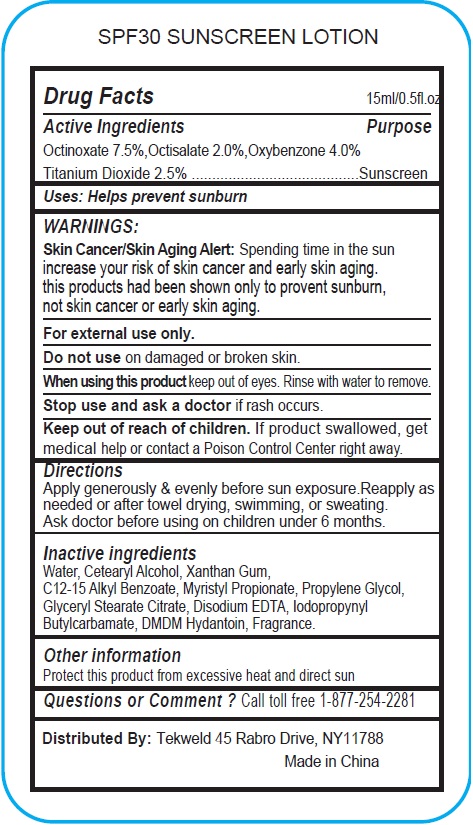 DRUG LABEL: SPF 30 SUNSCREEN
NDC: 71160-014 | Form: LOTION
Manufacturer: Tekweld Solutions, Inc.
Category: otc | Type: HUMAN OTC DRUG LABEL
Date: 20191226

ACTIVE INGREDIENTS: OCTINOXATE 75 mg/1 mL; OCTISALATE 20 mg/1 mL; OXYBENZONE 40 mg/1 mL; TITANIUM DIOXIDE 25 mg/1 mL
INACTIVE INGREDIENTS: WATER; CETOSTEARYL ALCOHOL; XANTHAN GUM; ALKYL (C12-15) BENZOATE; MYRISTYL PROPIONATE; PROPYLENE GLYCOL; GLYCERYL STEARATE CITRATE; EDETATE DISODIUM ANHYDROUS; IODOPROPYNYL BUTYLCARBAMATE; DMDM HYDANTOIN

SPF 30 SUNSCREEN LOTION

Active Ingredients

Octinoxate 7.5%,

Octisalate 2.0%,

Oxybenzone 4.0%

Titanium Dioxide 2.5%

Purpose

Sunscreen

Uses

• Helps prevent sunburn

WARNINGS:

Skin Cancer/Skin Aging Alert: Spending time in the sun increase your risk of skin cancer and early skin aging.
This products has been shown only to prevent sunburn, not skin cancer or early skin aging.

For external use only.

Do not use

on damaged or broken skin.

When using this product

keep out of eyes. Rinse with water to remove.

Stop use and ask a doctor

if rash occurs.

Keep out of reach of children.

If product swallowed, get medical help or contact a Poison Control Center right away.

Directions

Apply generously & evenly before sun exposure.Reapply as needed or after towel drying, swimming, or sweating. Ask doctor before using on children under 6 months.

Inactive ingredients

Water, Cetearyl Alcohol, Xanthan Gum, C12-15 Alkyl Benzoate, Myristyl Propionate, Propylene Glycol, Glyceryl Stearate Citrate, Disodium EDTA, Iodopropynyl Butylcarbamate, DMDM Hydantoin, Fragrance.

Other information

Protect this product from excessive heat and direct sun

Questions or Comment ?

Call toll free 1-877-254-2281

Distributed By:

Tekweld: 45 Rabro Drive, Hauppauge, NY11788